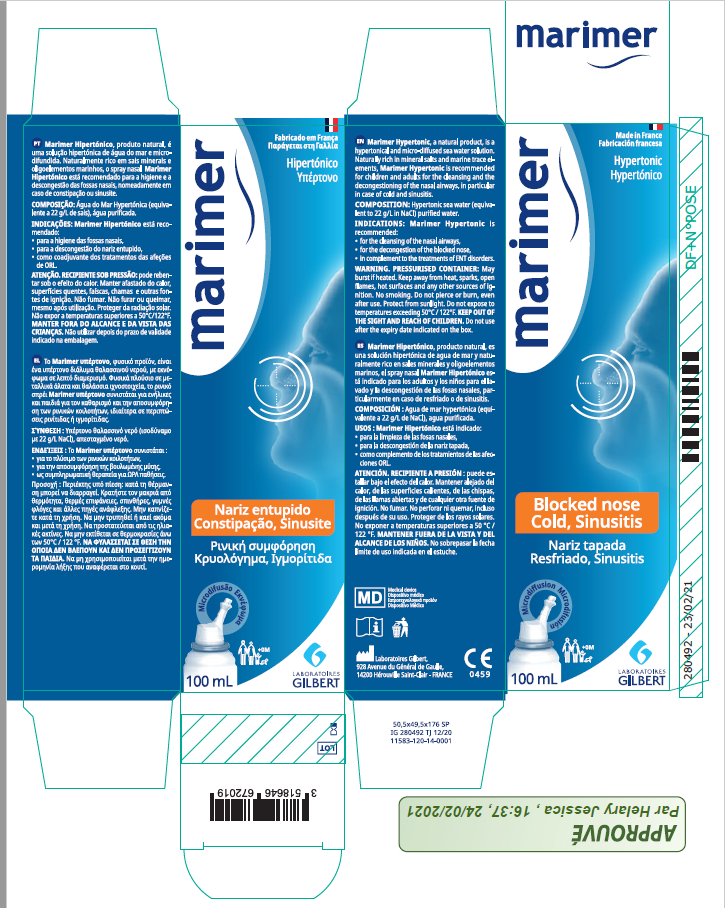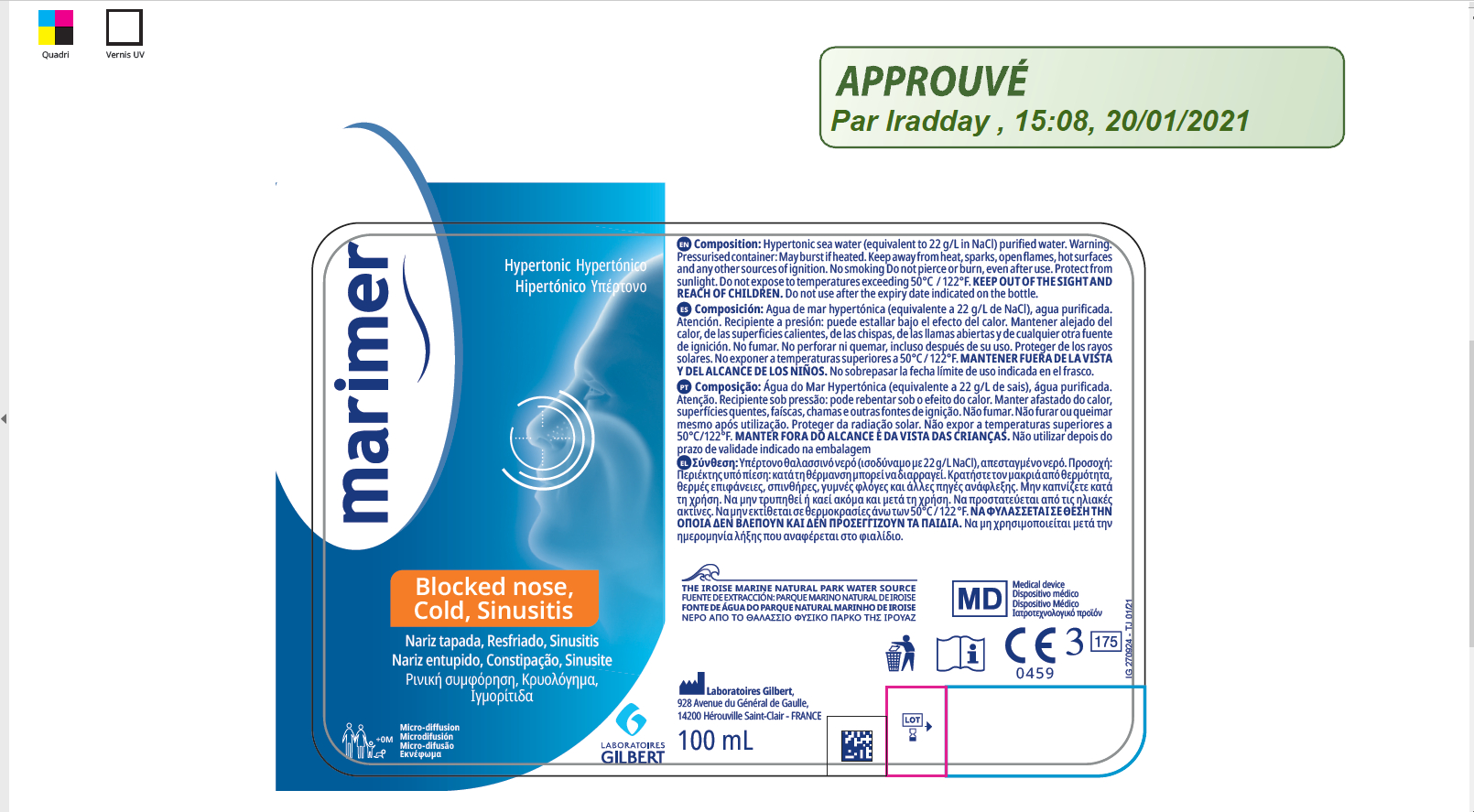 DRUG LABEL: Marimer Hypertonic Seawater Nasal
NDC: 82138-001 | Form: SPRAY
Manufacturer: LABORATOIRES GILBERT
Category: homeopathic | Type: HUMAN OTC DRUG LABEL
Date: 20210802

ACTIVE INGREDIENTS: SODIUM CHLORIDE 2.2 g/100 mL
INACTIVE INGREDIENTS: WATER

DOSAGE AND ADMINISTRATION

Marimer Hypertonic is recommended for children and adults for the cleansing and the decongestioning of the nasal airways, in particular in case of cold and sinusitis.

INACTIVE INGREDIENT

water

INDICATIONS AND USAGE

1.for the cleansing of the nasal airways
2.for the decongestion of the blocked nose,
3.in complement to the treatments of ENT disorders.

ACTIVE INGREDIENT

2.2% sodium chloride

KEEP OUT OFTHE SIGHT AND REACH OF CHILDREN

PURPOSE

recommended for children and adults for the cleansing

STORAGE AND HANDLING

Do not expose to temperatures exceeding 50°C/122°F

WARNINGS

May burst if heated.Keep away from heat, sparks, open flames, hot surfaces and any other sources of ignition. No smoking. Do not pierce or burn, even after use.Protect from sunlight. Do not expose to temperatures exceeding 5o°C/122°F. KEEP OUT OFTHE SIGHT AND REACH OF CHILDREN. Do not use after the expiry date indicated on the box.